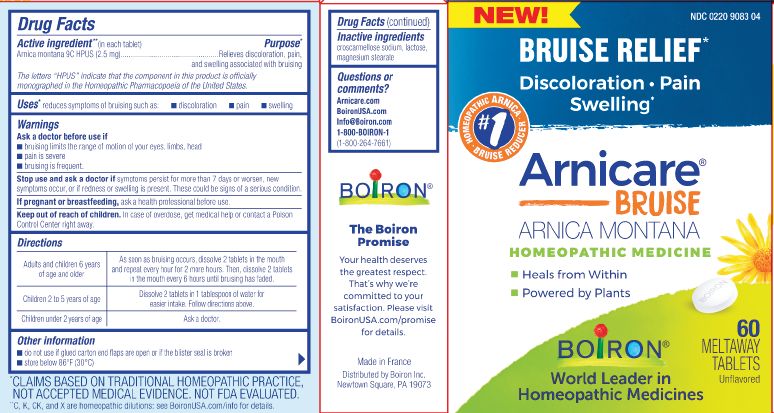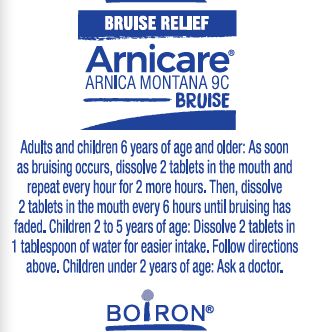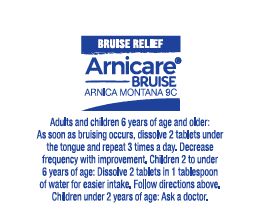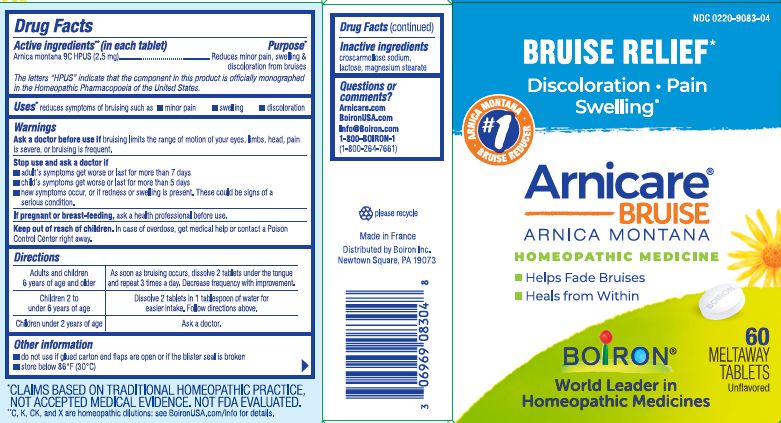 DRUG LABEL: Arnicare Bruise
NDC: 0220-9083 | Form: TABLET
Manufacturer: Boiron
Category: homeopathic | Type: HUMAN OTC DRUG LABEL
Date: 20250715

ACTIVE INGREDIENTS: ARNICA MONTANA 9 [hp_C]/1 1
INACTIVE INGREDIENTS: CROSCARMELLOSE SODIUM; MAGNESIUM STEARATE; LACTOSE, UNSPECIFIED FORM

Arnicare Bruise Tablets

Active ingredient** (in each tablet)

Arnica montana 9C HPUS (2.5 mg)

The letters "HPUS" indicate that the component in this product is officially monographed in the Homeopathic Pharmacopoeia of the United States.

Purpose*

Arnica montana 9C HPUS (2.5 mg) ... Reduces minor pain, swelling & discoloration from bruises

Uses*

reduces symptoms of bruising such as:

- minor pain
- swelling
- discoloration

Ask a doctor before use if bruising limits the range of motion of your eyes, limbs, head, pain is severe, or bruising is frequent.

Stop use and ask a doctor if

- adult's symptoms get worse or last more than 7 days
- child's symptoms get worse or last more than 5 days
- new symptoms occur, or if redness or swelling is present. These could be signs of a serious condition.

PREGNANCY OR BREAST FEEDING

If pregnant or breast-feeding, ask a health profession before use.

Keep out of reach of children. In case of overdose, get medical help or contact a Poison Control Center right away.

Directions

Adults and children 6 years of age and older - As soon as bruising occurs, dissolve 2 tablets under the tongue and repeat 3 times a day. Decrease frequency with improvement.

Children 2 to 6 years of age - Dissolve 2 tablets in 1 tablespoon of water for easier intake. Follow directions above.

Children under 2 years of age - Ask a doctor.

- do not use if glued carton end flaps are open or if the blister seal is broken
- store below 86° F (30° C)

60 meltaway tablets

Bruise relief*

Discoloration, Pain, Swelling*

No Known Drug Interactions

*CLAIMS BASED ON TRADITIONAL HOMEOPATHIC PRACTICE, NOT ACCEPTED MEDICAL EVIDENCE. NOT FDA EVALUATED.

**C,K,CK, and X are homeopathic dilutions: see BoironUSA.com/info for details.

INACTIVE INGREDIENT

croscarmellose sodium, lactose, magnesium stearate

QUESTIONS

Arnicare.com

BoironUSA.com

Info@Boiron.com

1-800-BOIRON-1

(1-800-264-7661)

Made in France

Distributed by Boiron Inc.

Newtown Square, PA 19073